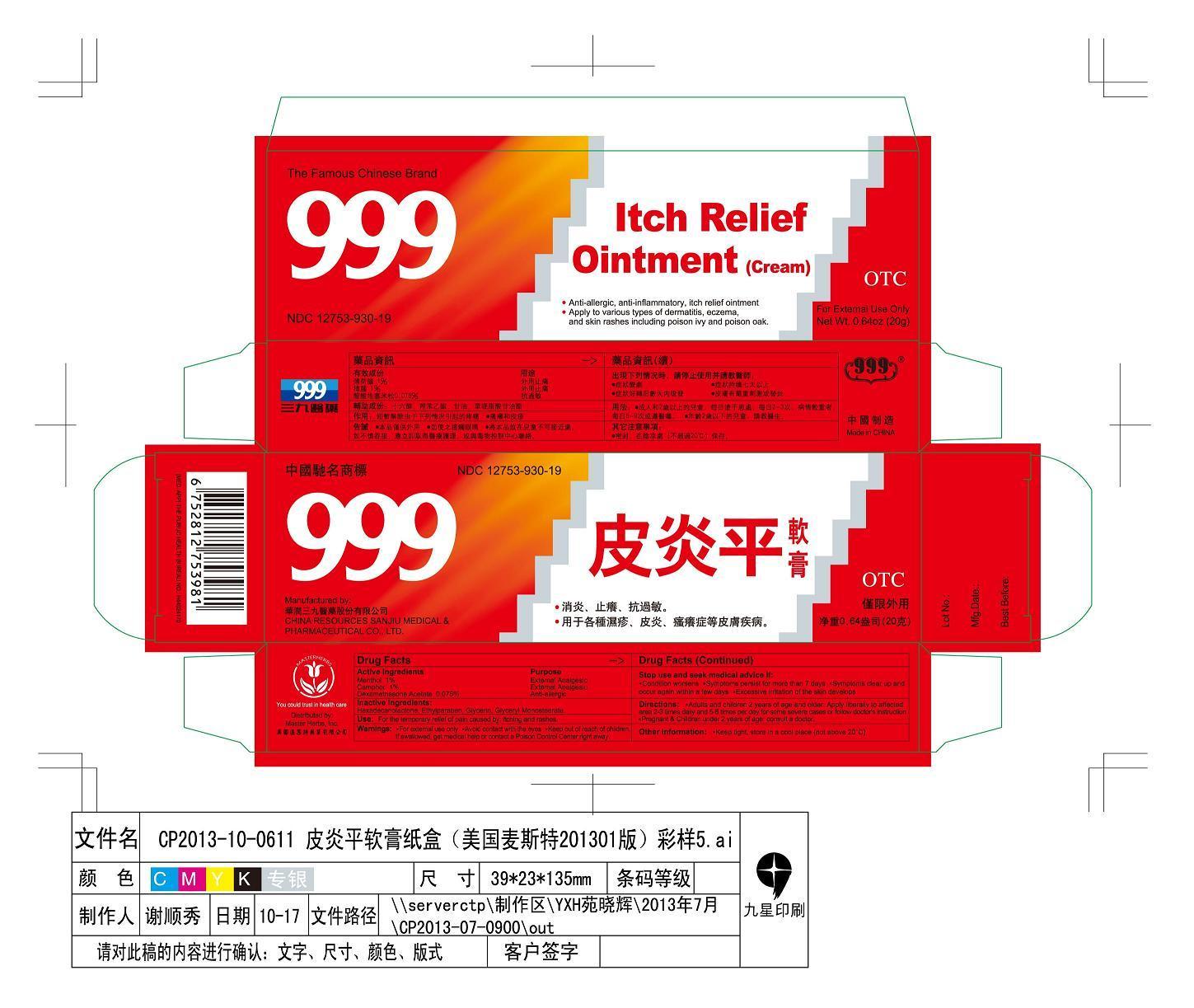 DRUG LABEL: 999 ITCH RELIEF
NDC: 12753-930 | Form: OINTMENT
Manufacturer: China Resources Sanjiu Medical & Pharmaceutical Co Ltd
Category: otc | Type: HUMAN OTC DRUG LABEL
Date: 20131022

ACTIVE INGREDIENTS: MENTHOL 200 mg/20000 mg; CAMPHOR (SYNTHETIC) 200 mg/20000 mg; DEXAMETHASONE 15 mg/20000 mg
INACTIVE INGREDIENTS: HEXADECANOLACTONE; Ethylparaben; Glycerin; Glyceryl Monostearate

999 ITCH RELIEF OINTMENT

ACTIVE INGREDIENTS

Menthol 1%

Camphor (synthetic) 1%

Dexamethasone Acetate 0.075%

Purpose

External Analgesic

External Analgesic

Anti-allergic

Warnings

For external use only. Avoid contact with the eyes. If swallowed, get medical help or contact a Poison Control Center right away.

Stop use and seek medical advice if

Condition worses. Symptoms persisit for more than 7 days. Symptoms clear up and occur again within a few days. Excessive irritation of the skin develops.

Directions

Pregnant and children under 2 years of age. Do not use, consult a doctor.

Warnings

Keep out of reach of children.

Directions

Adult and children 2 years of age and older. Apply liberally to affected area not more than 5 times daily and 5-8 times per day for some severe cases or follow doctor's instruction.

Other Information

Keep in a lightly closed container. Store at 8 to 30 degree centigrade (46-86 Fahrenheit) in a dry plac away from sunlight.

Inactive Ingredients

Hexadecanolactone

Ethylparaben

Glycerin

Glycertyl Monostearate